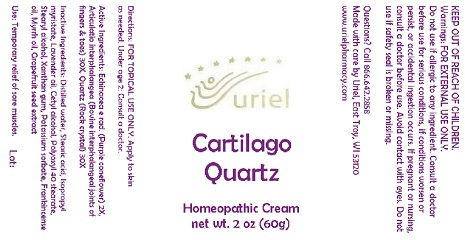 DRUG LABEL: Cartilago Quartz
NDC: 48951-3043 | Form: CREAM
Manufacturer: Uriel Pharmacy Inc.
Category: homeopathic | Type: HUMAN OTC DRUG LABEL
Date: 20170825

ACTIVE INGREDIENTS: ECHINACEA, UNSPECIFIED 2 [hp_X]/1 g; BEEF 30 [hp_X]/1 g; SILICON DIOXIDE 30 [hp_X]/1 g
INACTIVE INGREDIENTS: WATER; STEARIC ACID; ISOPROPYL MYRISTATE; LAVENDER OIL; CETYL ALCOHOL; POLYOXYL 40 STEARATE; STEARYL ALCOHOL; XANTHAN GUM; POTASSIUM SORBATE; FRANKINCENSE OIL; MYRRH OIL; CITRUS PARADISI SEED

Cartilago Quartz

INDICATIONS AND USAGE

Directions: FOR TOPICAL USE ONLY.

DOSAGE AND ADMINISTRATION

Apply to skin as needed. Under age 2: Consult a doctor.

ACTIVE INGREDIENT

Active Ingredients: Echinacea e rad. (Purple coneflower) 2X, Articulatio interphalangea (Bovine interphalangeal joints of fingers & toes) 30X, Quartz (Rock crystal) 30X

INACTIVE INGREDIENT

Inactive Ingredients: Distilled water, Stearic acid, Isopropyl myristate, Lavender oil, Cetyl alcohol, Polyoxyl 40 stearate, Stearyl alcohol, Xanthan gum, Potassium sorbate, Frankincense oil, Myrrh oil, Grapefruit seed extract

PURPOSE

Use: Temporary relief of sore muscles.

KEEP OUT OF REACH OF CHILDREN.

WARNINGS

Warnings: FOR EXTERNAL USE ONLY. Do not use if allergic to any ingredient. Consult a doctor before use for serious conditions, if conditions worsen or persist, or accidental ingestion occurs. If pregnant or nursing, consult a doctor before use. Avoid contact with eyes. Do not use if safety seal is broken or missing.

QUESTIONS

Questions? Call 866.642.2858 Made with care by Uriel, East Troy, WI 53120 www.urielpharmacy.com